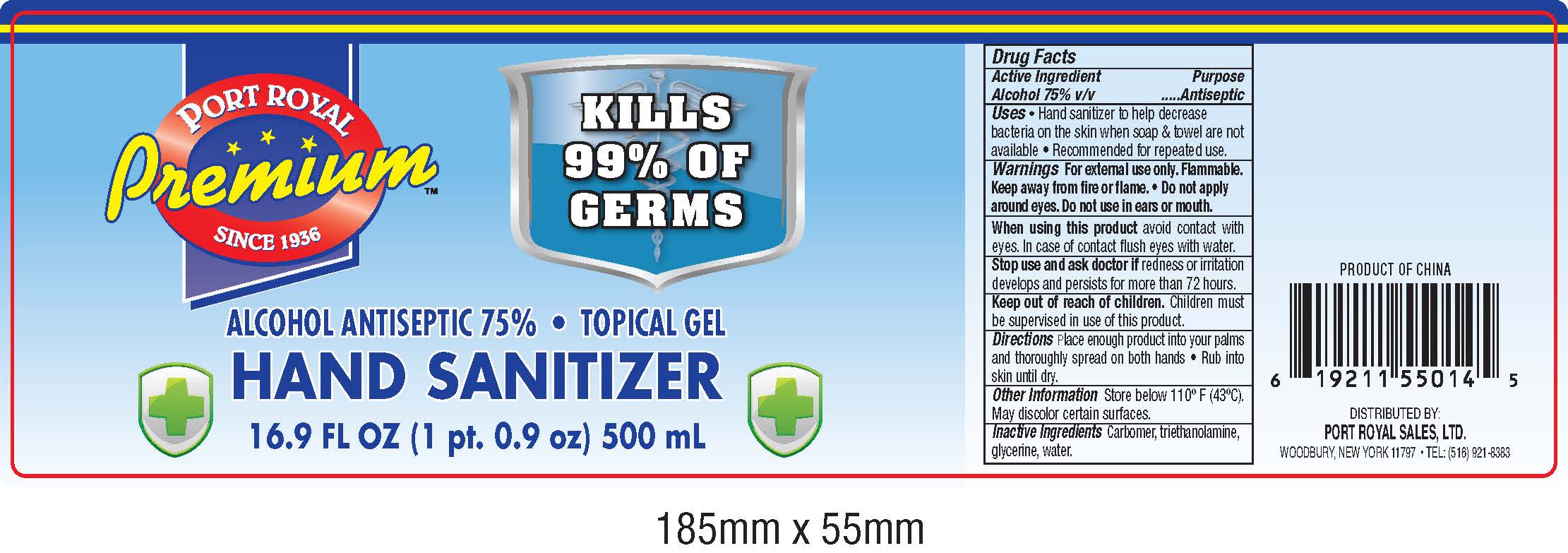 DRUG LABEL: Premium hand sanitrizer
NDC: 78620-001 | Form: GEL
Manufacturer: PORT ROYAL SALES, LTD.
Category: otc | Type: HUMAN OTC DRUG LABEL
Date: 20200622

ACTIVE INGREDIENTS: ALCOHOL 75 mL/100 mL
INACTIVE INGREDIENTS: CARBOMER HOMOPOLYMER, UNSPECIFIED TYPE; WATER; TROLAMINE; GLYCERIN

Premium Port Royal Hand Sanitizer75

Active Ingredient

Alcohol 75% v/v.

Purpose

Antiseptic

Uses

• Hand sanitizer to help decrease bacteria on the skin when soap and towel are not available. • Recommended for repeated use

Warnings

For external use only. Flammable. Keep away from heat or flame • Do not apply around eyes • Do not use in ears or mouth

When using this product

avoid contact eith eyes. In case of eye contact flush eyes with water

Stop use and ask a doctor if

redness or irritation develops and persists for more than 72 hours.

Keep out of reach of children

Children must be supervised in use of this product.

Directions

Place enough product into your palms and thoroughly spread on both hands. • Rub into skin until dry.

Other information

Store below 110ºF (43ºC). May discolor certain surfaces.

Inactive ingredients

Carbomer, triethanolamine, glycerine, water.